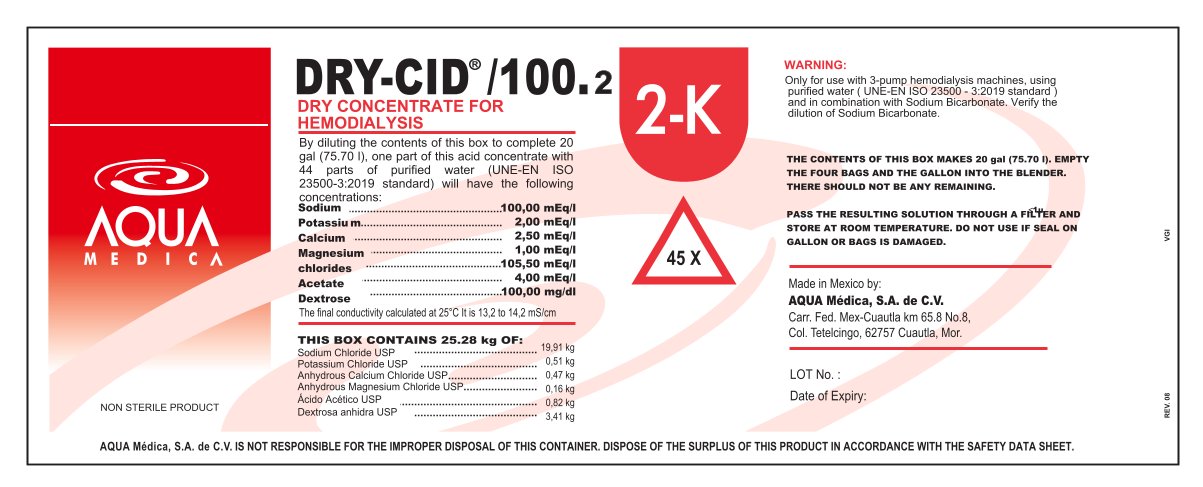 DRUG LABEL: DRY-CID
NDC: 81943-601 | Form: POWDER, FOR SOLUTION
Manufacturer: Aqua Medica, S.A. de C.V.
Category: otc | Type: HUMAN OTC DRUG LABEL
Date: 20251110

ACTIVE INGREDIENTS: POTASSIUM CHLORATE 0.51 kg/100 kg
INACTIVE INGREDIENTS: SODIUM CHLORIDE 19.91 kg/100 kg; CALCIUM CHLORIDE ANHYDROUS 0.47 kg/100 kg; MAGNESIUM CHLORIDE ANHYDROUS 0.16 kg/100 kg; ACETIC ACID 0.82 kg/100 kg; ANHYDROUS DEXTROSE 3.41 kg/100 kg; WATER

By diluting the contents of this box to complete 20
gal (75.70 l), one part of this acid concentrate with
44 parts of purified water (UNE-EN ISO
23500-3:2019 standard) will have the following
concentrations:
Sodium
Potassiu m
Calcium
Magnesium
chlorides
Acetate
Dextrose
The final conductivity calculated at 25°C It is 13,2 to 14,2 mS/cm
NON STERILE PRODUCT
100,00 mEq/l
2,00 mEq/l
2,50 mEq/l
1,00 mEq/l
105,50 mEq/l
4,00 mEq/l
100,00 mg/dl

ACTIVE INGREDIENT

Potassium Chlorate

PURPOSE

For use with 3-pump hemodialysis machines only.

INDICATIONS AND USAGE

For use with 3-pump hemodialysis machines only, using purified water (Standard 13959:2014) and in conbination with

WARNINGS

For use with 3-pump hemodialysis machines only.

DO NOT USE

If the warranty seal is damaged or broken and do not allow debris to fall into the concentrate.

WHEN USING

Using purified water (Standard 13959:2014) and in conbination with sodium bicarbonate.

STOP USE

If you do not use the entire contents, discard the excess.

Keep out of reach of children. If swallowed, get medical help or contact a Poison Control Center right away.

DOSAGE AND ADMINISTRATION

By diluting one part of this acid concentrate with 44 parts of purified water (ISO Standard 13959:2014).

STORAGE AND HANDLING

Store at room temperature.

Keep container tightly closed when not in use.

INACTIVE INGREDIENT

Sodium Chloride, Anhydrous Calcium Chloride, Anhydrous Magnesium Chloride, Acetic Acid, Dextrosa

PACKAGE LABEL

81943-601-01